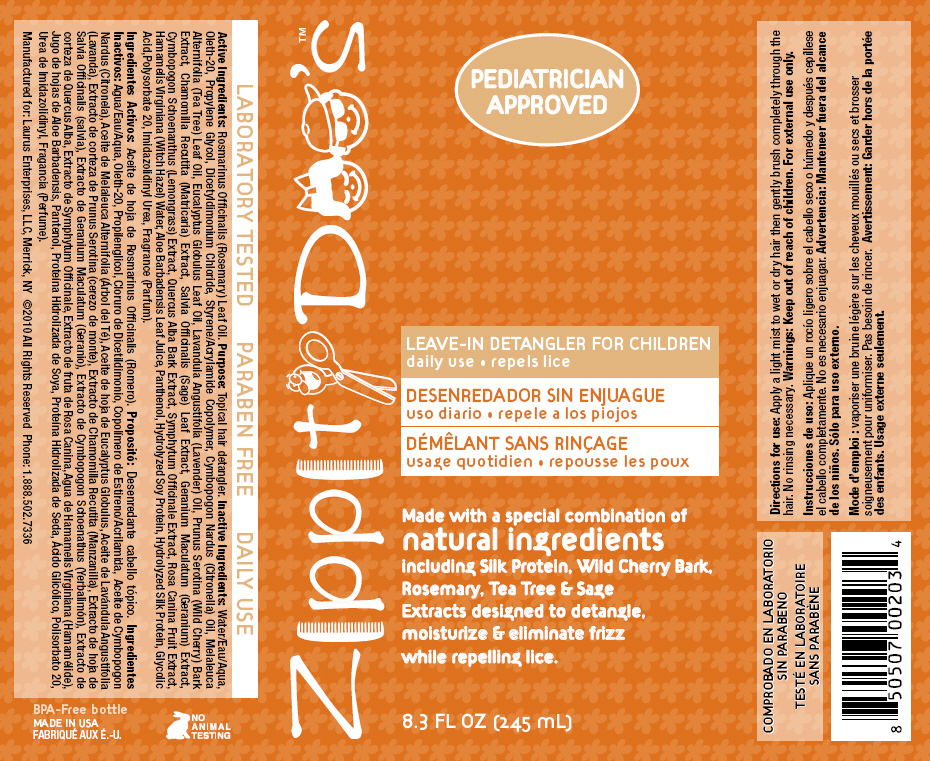 DRUG LABEL: Zippity Doos 
NDC: 57240-2034 | Form: SPRAY
Manufacturer: Laurus Enterprises, LLC
Category: homeopathic | Type: HUMAN OTC DRUG LABEL
Date: 20130404

ACTIVE INGREDIENTS: Rosemary Oil 2.45 mg/1 mL
INACTIVE INGREDIENTS: Water; Oleth-20; Propylene Glycol; Dicetyldimonium Chloride; Citronella Oil; Tea Tree Oil; Eucalyptus Oil; Lavender Oil; Prunus Serotina Bark; Matricaria Recutita; Sage; Geranium Maculatum Root; Cymbopogon Schoenanthus Top; Quercus Alba Bark; Rosa Canina Fruit; Hamamelis Virginiana Top; Aloe Vera Leaf; Panthenol; Glycolic Acid; Polysorbate 20; Imidurea

Zippity Doo's™
LEAVE-IN DETANGLER FOR CHILDREN

Active Ingredients

Rosmarinus Officinalis (Rosemary) Leaf Oil.

Purpose

PURPOSE

Topical hair detangler.

Inactive Ingredients

Water/Eau/Aqua, Oleth-20, Propylene Glycol, Dicetyldimonium Chloride, Styrene/Acrylamide Copolymer, Cymbopogon Nardus (Citronella) Oil, Melaleuca Alternifolia (Tea Tree) Leaf Oil, Eucalyptus Globulus Leaf Oil, Lavandula Angustifolia (Lavender) Oil, Prunus Serotina (Wild Cherry) Bark Extract, Chamomilla Recutita (Matricaria) Extract, Salvia Officinalis (Sage) Leaf Extract, Geranium Maculatum (Geranium) Extract, Cymbopogon Schoenanthus (Lemongrass) Extract, Quercus Alba Bark Extract, Symphytum Officinale Extract, Rosa Canina Fruit Extract, Hamamelis Virginiana (Witch Hazel) Water, Aloe Barbadensis Leaf Juice, Panthenol, Hydrolyzed Soy Protein, Hydrolyzed Silk Protein, Glycolic Acid,Polysorbate 20, Imidazolidinyl Urea, Fragrance (Parfum).

Directions for use

Apply a light mist to wet or dry hair then gently brush completely through the hair. No rinsing necessary.

PRINCIPAL DISPLAY PANEL - 245 mL Bottle Label

Zippity Doo's™

PEDIATRICIAN
APPROVED

LEAVE-IN DETANGLER FOR CHILDREN
daily use • repels lice

Made with a special combination of
natural ingredients
including Silk Protein, Wild Cherry Bark,
Rosemary, Tea Tree & Sage
Extracts designed to detangle,
moisturize & eliminate frizz
while repelling lice.

8.3 FL OZ (245 mL)